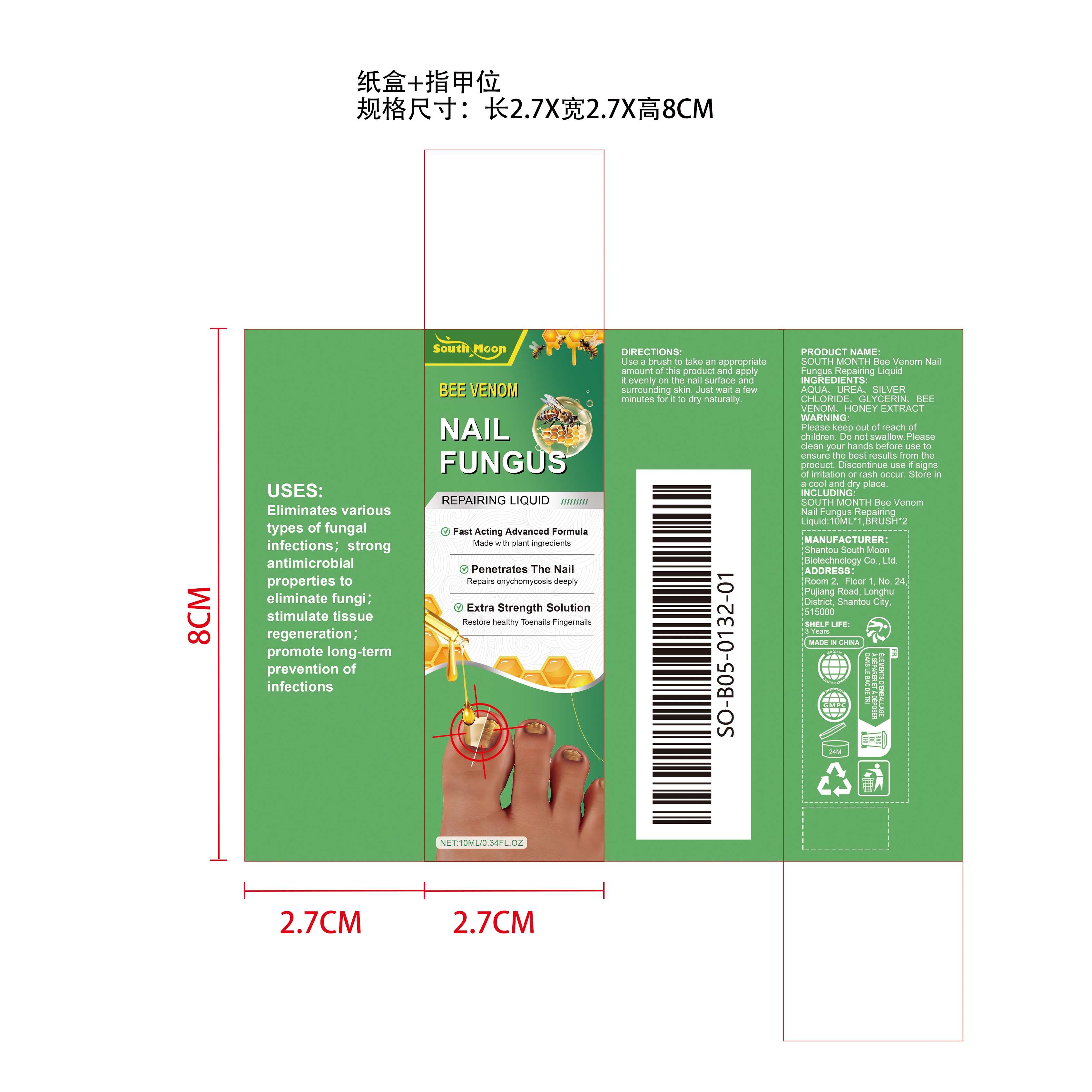 DRUG LABEL: SOUTH MOON Bee Venom Nail Fungus Repairing Liquid
NDC: 84983-004 | Form: LIQUID
Manufacturer: Shantou South Moon Biotechnology Co., Ltd.
Category: otc | Type: HUMAN OTC DRUG LABEL
Date: 20251127

ACTIVE INGREDIENTS: APIS MELLIFERA VENOM 0.002 g/10 g; HONEY 0.002 g/10 g
INACTIVE INGREDIENTS: SILVER CHLORIDE 0.05 g/10 g; AQUA 9.444 g/10 g; UREA 0.5 g/10 g; GLYCERIN 0.002 g/10 g

ACTIVE INGREDIENTS

APIS MELLIFERA VENOM、HONEY

PURPOSE

Eliminates various types of fungal infections；strong antimicrobial properties to eliminate fungi；stimulate tissue regeneration；promote long-term prevention of infections

USES

Use a brush to take an appropriate amount of this product and apply it evenly on the nail surface and surrounding skin. Just wait a few minutes for it to dry naturally.

Warnings

Please keep out of reach of children. Do not swallow.Please clean your hands before use to ensure the best results from the product. Discontinue use if signs of irritation or rash occur. Store in a cool and dry place.

Do not use

Discontinue use if signs of irritation or rash occur.

Stop use

Discontinue use if signs of irritation or rash occur.

KEEP OUT OF REACH OF CHILDREN

Please keep out of reach of children. Do not swallow.

STORAGE AND HANDLING

Store in a cool and dry place.

INACTIVE INGREDIENTS

AQUA、
UREA、
SILVER CHLORIDE、
GLYCERIN